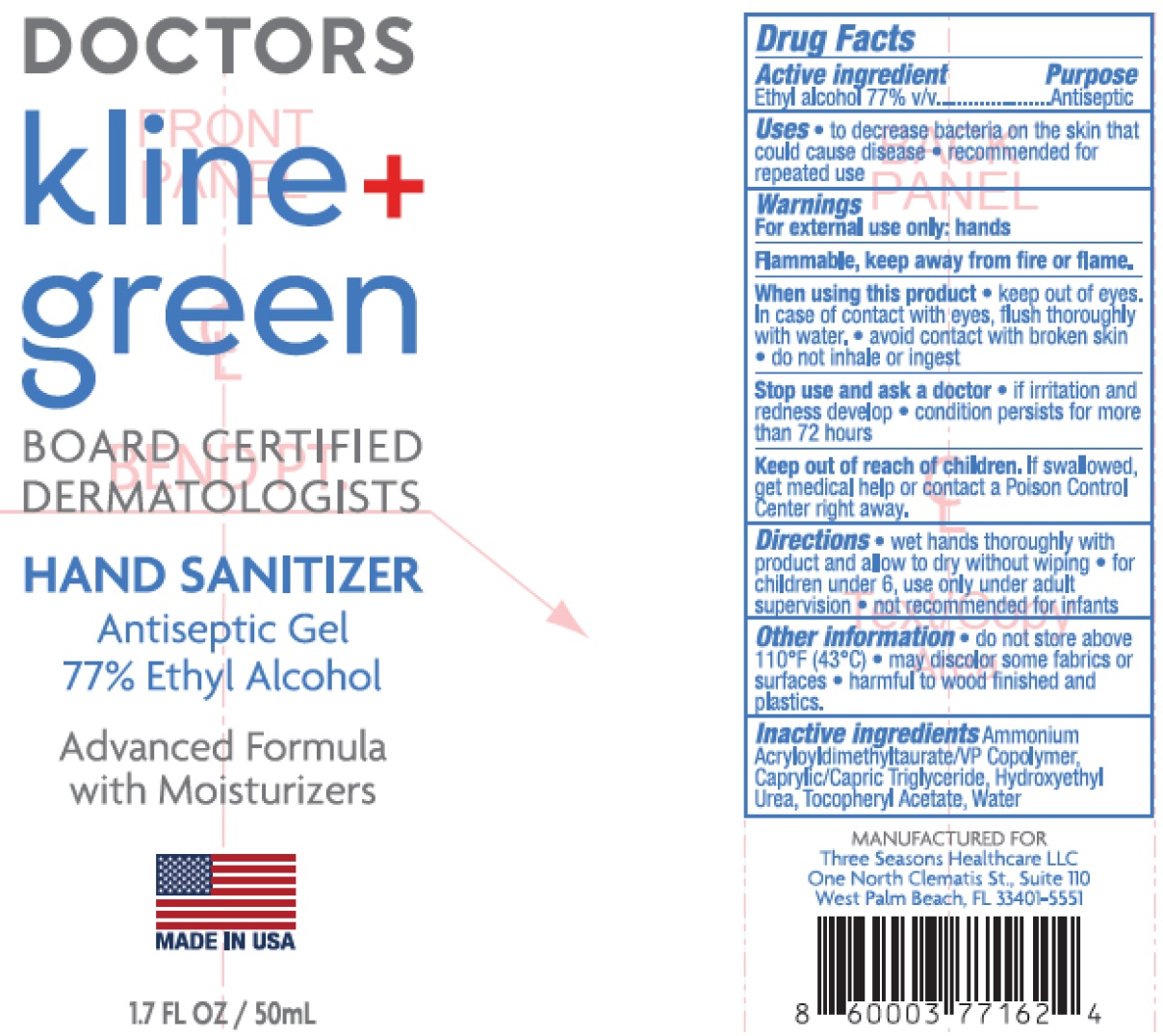 DRUG LABEL: Doctors Kline and Green Board Certified Dermatologist Hand Sanitizer
NDC: 23667-103 | Form: GEL
Manufacturer: Formulated Solutions, LLC
Category: otc | Type: HUMAN OTC DRUG LABEL
Date: 20231129

ACTIVE INGREDIENTS: ALCOHOL 77 mL/100 mL
INACTIVE INGREDIENTS: AMMONIUM ACRYLOYLDIMETHYLTAURATE/VP COPOLYMER; MEDIUM-CHAIN TRIGLYCERIDES; HYDROXYETHYL UREA; .ALPHA.-TOCOPHEROL ACETATE; WATER

Doctors Kline & Green Board Certified Dermatologist Hand Sanitizer

Active ingredient

Ethyl alcohol 77% v/v

Purpose

Antiseptic

Uses

- to decrease bacteria on the skin that could cause disease
- recommended for repeated use

Warnings

For external use only:hands

Flammable, keep away from fire or flame.

When using this product

- keep out of eyes. In case of contact with eyes, flush thoroughly with water.
- avoid contact with broken skin
- do not inhale or ingest

Stop use and ask a doctor

- if irritation and redness develop
- condition persists for more than 72 hours

Keep out of reach of children.

If swallowed, get medical help or contact a Poison Control Center right away.

Directions

- wet hands thoroughly with product and allow to dry without wiping
- for children under 6, use only under adult supervision
- not recommended for infants

Other information

- do not store above 110°F (43°C)
- may discolor some fabrics or surfaces
- harmful to wood finished and plastics.

Inactive ingredients

Ammonium Acryloyldimethyltaurate/VP Copolymer, Caprylic/ Capric Triglyceride, HYdroxyethyl Urea, Tocopheryl Acetate, Water